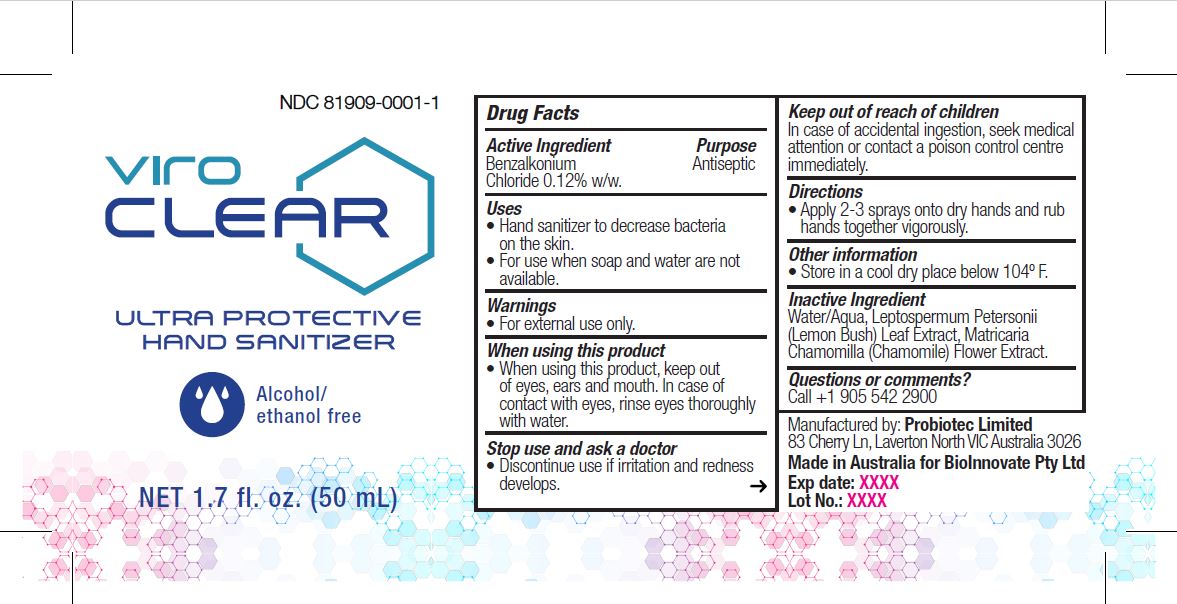 DRUG LABEL: ViroCLEAR
NDC: 81909-0001 | Form: LIQUID
Manufacturer: Bioinnovate Pty Ltd
Category: otc | Type: HUMAN OTC DRUG LABEL
Date: 20210607

ACTIVE INGREDIENTS: BENZALKONIUM CHLORIDE 0.12 g/100 mL
INACTIVE INGREDIENTS: LEPTOSPERMUM PETERSONII LEAF OIL; CHAMOMILE; WATER

Active Ingredient

Benzalkonium Chloride 0.12% w/w.

Purpose

Antiseptic, Hand Sanitizer

Uses

- Hand sanitizer to decrease bacteria on the skin.
- For use when soap and water are not available.

Warnings

For external use only.

When using this product, keep out of eyes, ears and mouth. In case ofcontact with eyes, rinse eyes thoroughly with water.

Stop use and ask a doctor

Discontinue use if irritation and redness develops.

Keep out of reach of children

In case of accidental ingestion, seek medical attention or contact a poison control centre immediately.

Directions

Apply 2-3 sprays onto dry hands and rub hands together vigorously.

Other information

Store in a cool dry place below 104º F.

Inactive Ingredients

Water/Aqua, Leptospermum Petersonii (Lemon Bush) Leaf Extract, Matricaria Chamomilla (Chamomile) Flower Extract.

Questions or comments

Call +1 905 542 2900

Package Label - Principal Display Panel

50 mL; NDC 81909-0001-1